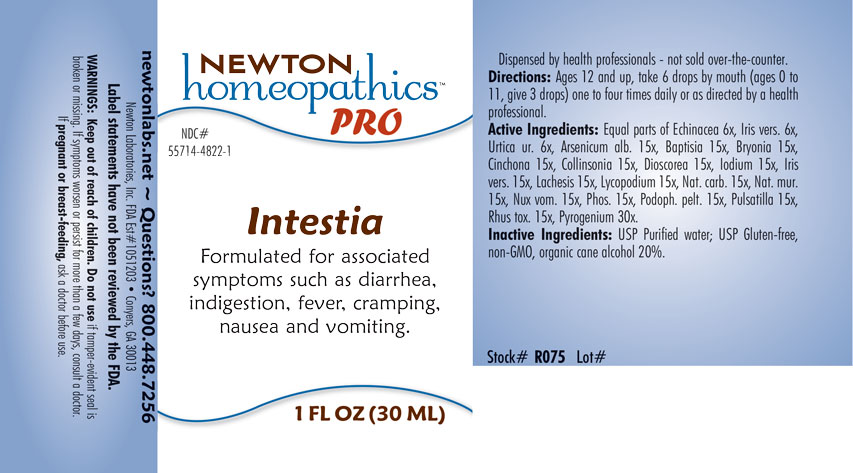 DRUG LABEL: Intestia
NDC: 55714-4822 | Form: LIQUID
Manufacturer: Newton Laboratories, Inc.
Category: homeopathic | Type: HUMAN OTC DRUG LABEL
Date: 20201204

ACTIVE INGREDIENTS: ECHINACEA, UNSPECIFIED 6 [hp_X]/1 mL; ANEMONE PULSATILLA 15 [hp_X]/1 mL; ARSENIC TRIOXIDE 15 [hp_X]/1 mL; BAPTISIA TINCTORIA ROOT 15 [hp_X]/1 mL; BRYONIA ALBA ROOT 15 [hp_X]/1 mL; CINCHONA OFFICINALIS BARK 15 [hp_X]/1 mL; COLLINSONIA CANADENSIS ROOT 15 [hp_X]/1 mL; DIOSCOREA VILLOSA TUBER 15 [hp_X]/1 mL; IODINE 15 [hp_X]/1 mL; IRIS VERSICOLOR ROOT 15 [hp_X]/1 mL; LACHESIS MUTA VENOM 15 [hp_X]/1 mL; LYCOPODIUM CLAVATUM SPORE 15 [hp_X]/1 mL; SODIUM CARBONATE 15 [hp_X]/1 mL; SODIUM CHLORIDE 15 [hp_X]/1 mL; STRYCHNOS NUX-VOMICA SEED 15 [hp_X]/1 mL; PHOSPHORUS 15 [hp_X]/1 mL; PODOPHYLLUM 15 [hp_X]/1 mL; URTICA URENS 6 [hp_X]/1 mL; TOXICODENDRON PUBESCENS LEAF 15 [hp_X]/1 mL; RANCID BEEF 30 [hp_X]/1 mL
INACTIVE INGREDIENTS: WATER; ALCOHOL

Intestia 4822L

INDICATIONS & USAGE SECTION

Formulated for associated symptoms such as diarrhea, indigestion, fever, cramping, nausea and vomiting.

DOSAGE & ADMINISTRATION SECTION

Directions: Ages 12 and up, take 6 drops by mouth (ages 0 to 11, give 3 drops) one to four times daily or as directed by a health professional.

OTC - ACTIVE INGREDIENT SECTION

Equal parts of Echinacea 6x, Iris versicolor 6x Urtica urens 6x, Arsenicum album 15x, Baptisia tinctoria 15x, Bryonia 15x, Cinchona officinalis 15x, Collinsonia canadensis 15x, Dioscorea villosa 15, Iodium 15x, Iris versicolor 15x, Lachesis mutus 15x, Lycopodium clavatum 15x, Natrum carbonicum 15x, Natrum muriaticum 15x, Nux vomica 15x, Phosphorus 15x, Podophyllum peltatum 15x, Pulsatilla 15x, Rhus toxicodendron 15x, Pyrogenium 30x.

OTC - PURPOSE SECTION

Formulated for associated symptoms such as diarrhea, indigestion, fever, cramping, nausea and vomiting.

INACTIVE INGREDIENT SECTION

Inactive Ingredients: USP Purified Water; USP Gluten-free, non-GMO, organic cane alcohol 20%.

QUESTIONS SECTION

newtonlabs.net - Questions? 800.448.7256

Newton Laboratories, Inc. FDA Est # 1051203 Conyers, GA 30013

WARNINGS SECTION

WARNINGS: Keep out of reach of children. Do not use if tamper-evident seal is broken or missing. If symptoms worsen or persist for more than a few days, consult a doctor. If pregnant or breast-feeding, ask a doctor before use.

OTC - PREGNANCY OR BREAST FEEDING SECTION

If pregnant or breast-feeding, ask a doctor before use.

OTC - KEEP OUT OF REACH OF CHILDREN SECTION

Keep out of reach of children.